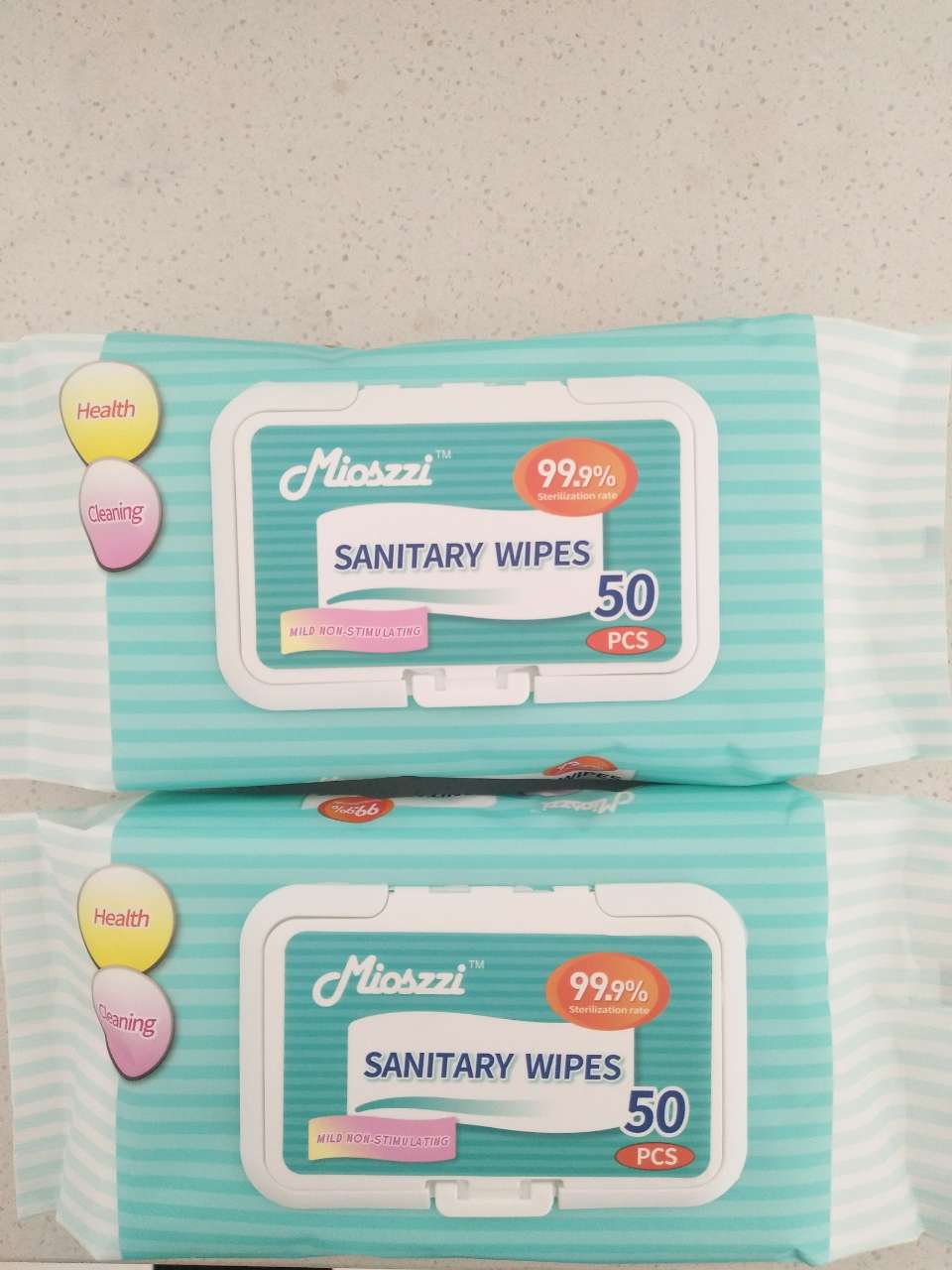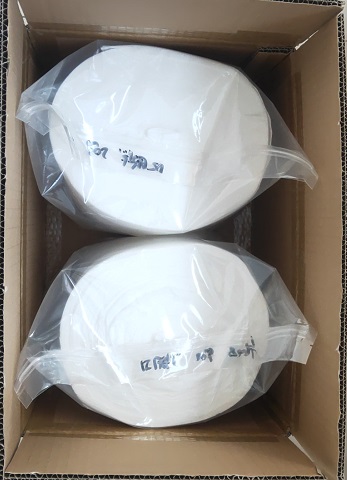 DRUG LABEL: Mioszzi SANITARY WIPES
NDC: 75269-014 | Form: CLOTH
Manufacturer: LINGHAI ZHANWANG BIOTECHNOLOGY CO.,LTD.
Category: otc | Type: HUMAN OTC DRUG LABEL
Date: 20241228

ACTIVE INGREDIENTS: BENZALKONIUM CHLORIDE 0.04 g/100 g
INACTIVE INGREDIENTS: ETHYLHEXYLGLYCERIN; PROPYLENE GLYCOL; METHYLPARABEN; PHENOXYETHANOL; WATER

75269-014 Mioszzi SANITARY WIPES

ACTIVE INGREDIENT

benzalkonium chloride 0.035%-0.045% (W/W)

PURPOSE

Kill 99.9% E. coli and staphylococcus aureus

Usage:

Opean the seal sticker and take the wipes, please avoid using on the wound.

Notes:

1.At room temperature in storage. Keep away from heat and avoid direct sunlight.

2.This wipe will not be insoluble in water. Please don't throw it into the toilet.

3.Children should use it under the adult supervision to keep from eating it.

4.Please discontinue use it if sensitive condition occurs.

KEEP OUT OF REACH OF CHILDREN

Children should use it under the adult supervision to keep from eating it.

DOSAGE AND ADMINISTRATION

Usage: Opean the seal sticker and take the wipes, please avoid using on the wound.

STORAGE AND HANDLING

At room temperature in storage. Keep away from heat and avoid direct sunlight.

Shelf Life: 2 Years,

Size: 160mmx180mm

INACTIVE INGREDIENT

Ingredients: Non-woven spunlace fabric, RO water

PDP

50PCS, NDC: 75269-014-01

PACKAGE LABEL

2000 PCS

NDC: 75269-014-02